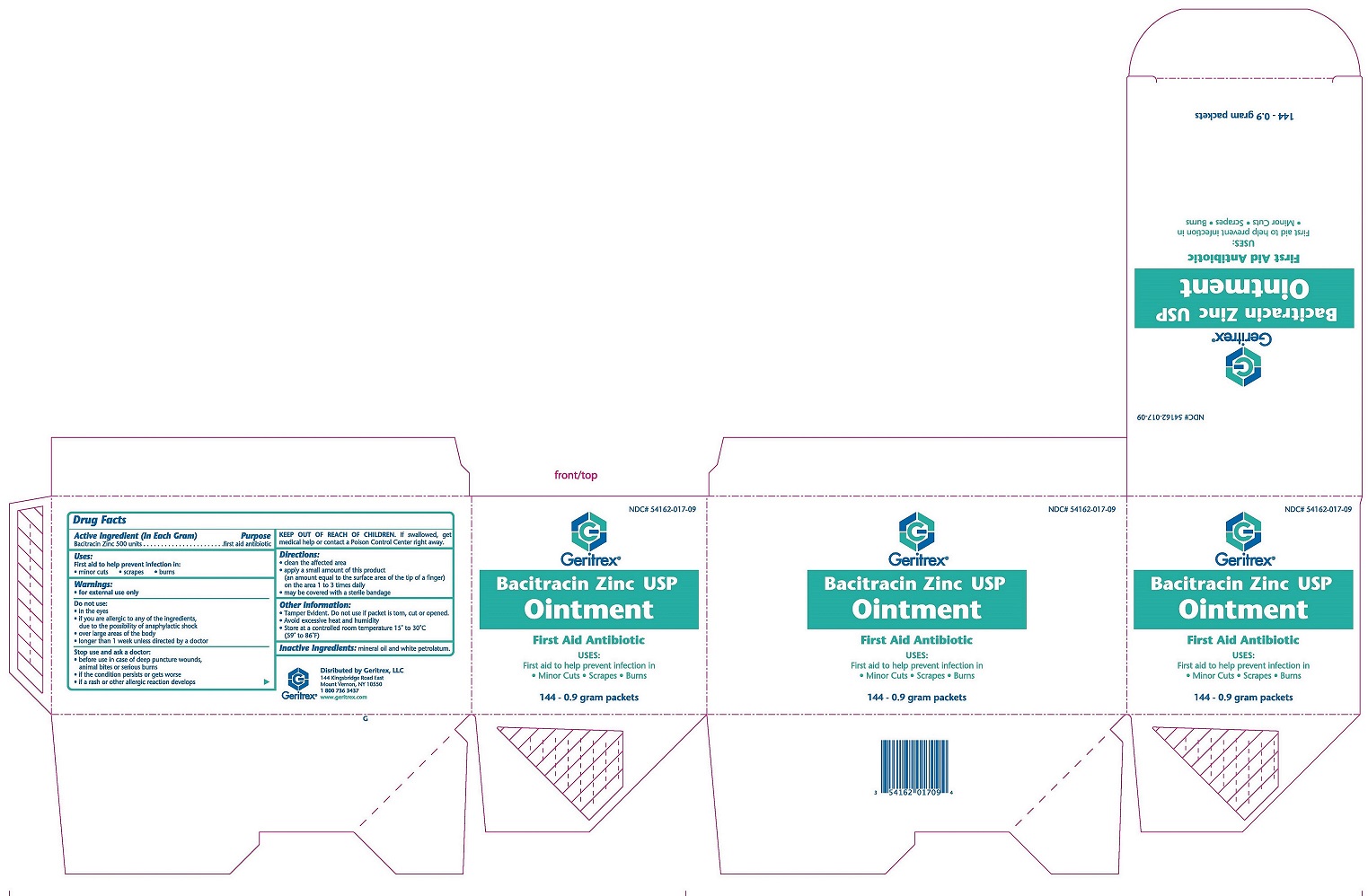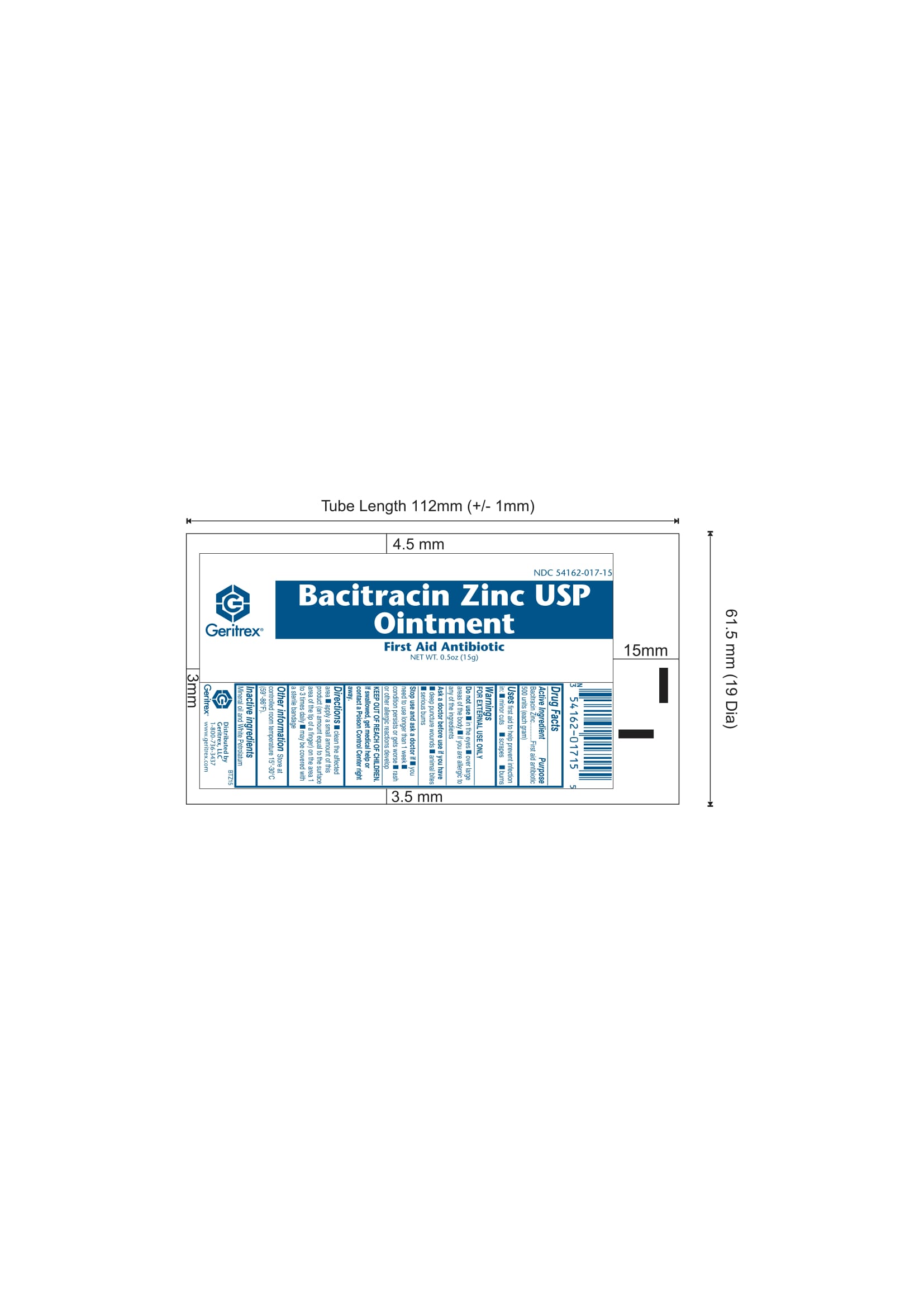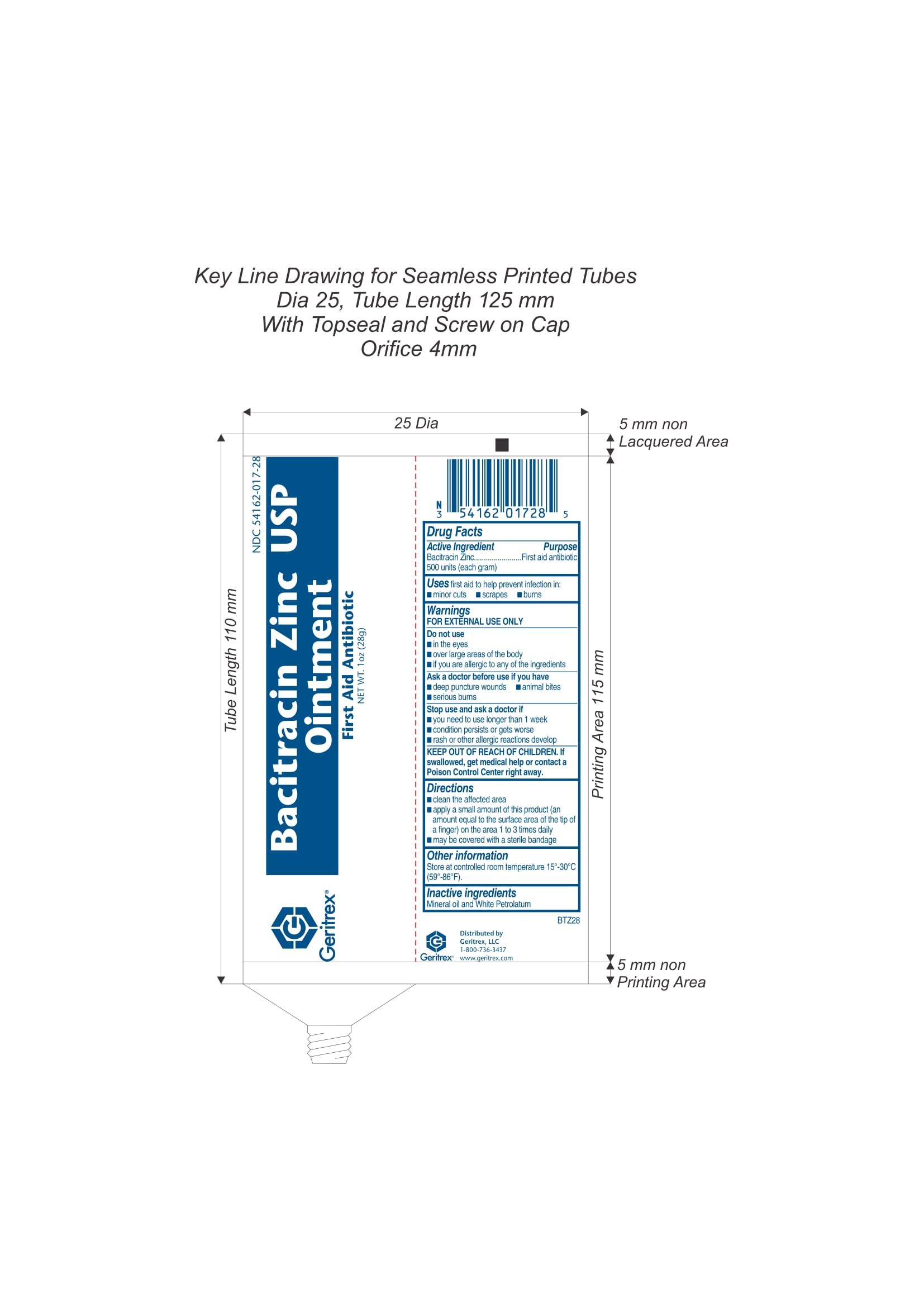 DRUG LABEL: Bacitracin Zinc
NDC: 54162-017 | Form: OINTMENT
Manufacturer: GERITREX LLC
Category: otc | Type: HUMAN OTC DRUG LABEL
Date: 20180117

ACTIVE INGREDIENTS: BACITRACIN ZINC 500 [iU]/1 g
INACTIVE INGREDIENTS: MINERAL OIL; PETROLATUM

Bacitracin Zinc USP Ointment

Active Ingredient: Purpose:

Bacitracin Zinc 500 units (each gram)....................First Aid Antibiotic

Uses:

Helps prevent infection in: Minor cuts, scrapes, and/or burns

Warnings:

FOR EXTERNAL USE ONLY
Allergy Alert: Do not use if allergic to any of the ingredients.
Do not use in eyes or on large areas of the body.
Ask a doctor before use if you have deep or puncture wounds, animal bites or serious burns.
When using this product, do not use longer than 1 week, unless directed by a doctor.
Stop use and ask a doctor if condition lasts or gets worse, rahs or other allergic reaction develops.

KEEP OUT OF REACH OF CHILDREN
In the event of accidental ingestion, contact a Poison Control Center right away.

Directions:

Clean affected area. Apply a small amount (equal to surface area of tip of finger) on area 1 to 3 times daily. May be covered with a sterile bandage.

Inactive Ingredients:

Mineral Oil and White Petrolatum

Other Information:

Store at controlled room temperature
59°-86°F (15°-30°C).